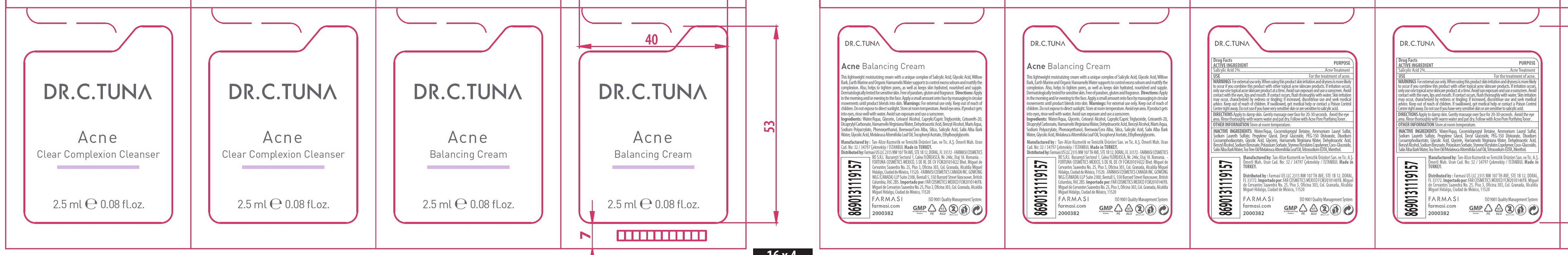 DRUG LABEL: Dr. C. Tuna Acne Clear Complexion Cleanser
NDC: 74690-021 | Form: KIT | Route: TOPICAL
Manufacturer: Farmasi US LLC
Category: otc | Type: HUMAN OTC DRUG LABEL
Date: 20231105

ACTIVE INGREDIENTS: SALICYLIC ACID 20 mg/1 mL
INACTIVE INGREDIENTS: WATER; COCAMIDOPROPYL BETAINE; AMMONIUM LAURYL SULFATE; SODIUM LAURETH SULFATE; PROPYLENE GLYCOL; DECYL GLUCOSIDE; PEG-150 DISTEARATE; DISODIUM COCOAMPHODIACETATE; GLYCOLIC ACID; GLYCERIN; DEHYDROACETIC ACID; BENZYL ALCOHOL; SODIUM BENZOATE; POTASSIUM SORBATE; COCO GLUCOSIDE; SALIX ALBA BARK VOLATILE OIL; TEA TREE OIL; EDETATE SODIUM; MENTHOL

Dr. C. Tuna Acne Clear Complexion Cleanser

ACTIVE INGREDIENT

Salicylic Acid 2%

PURPOSE

Acne Treatment

USE

For the treatment of acne.

WARNINGS

For external use only.

When using this product

skin irritation and dryness is more likely to occur if you combine this product with other topical acne skincare products. If irritation occurs, only use one topical acne skincare product at a time. Avoid sun exposure and use a sunscreen. Avoid contact with the eyes, lips and mouth. If contact occurs, flush thoroughly with water. Skin irritation may occur, characterized by redness or tingling; if increased, discontinue use and seek medical advice.

Keep out of reach of children.

If swallowed, get medical help or contact a Poison Control Center right away. Do not use if you have very sensitive skin or are sensitive to salicylic acid.

DIRECTIONS

Apply to damp skin. Gently massage over face for 20-30 seconds. Avoid the eye area. Rinse thoroughly with warm water and pat dry. Follow with Acne Pore Purifying Toner.

OTHER INFORMATION

Store at room temperature.

INACTIVE INGREDIENTS:

Water/Aqua, Cocomidopropyl Betaine, Ammonium Lauryl Sulfat, Sodium Laureth Sulfate, Propylene Glycol, Decyl Glucoside, PEG-150 Distearate, Disodium Cocoamphodiacetate, Glycolic Acid, Glycerin, Hamamelis Virginiana Water, Dehydroacetic Acid, Benzyl Alcohol, Sodium Benzoate, Potassium Sorbate, Styrene/Acrylates Copolymer, Coco-Glucoside, Salix Alba Bark Water, Tea Tree Oil/Melaleuca Alternifolia Leaf Oil, Tetrasodium EDTA, Menthol.